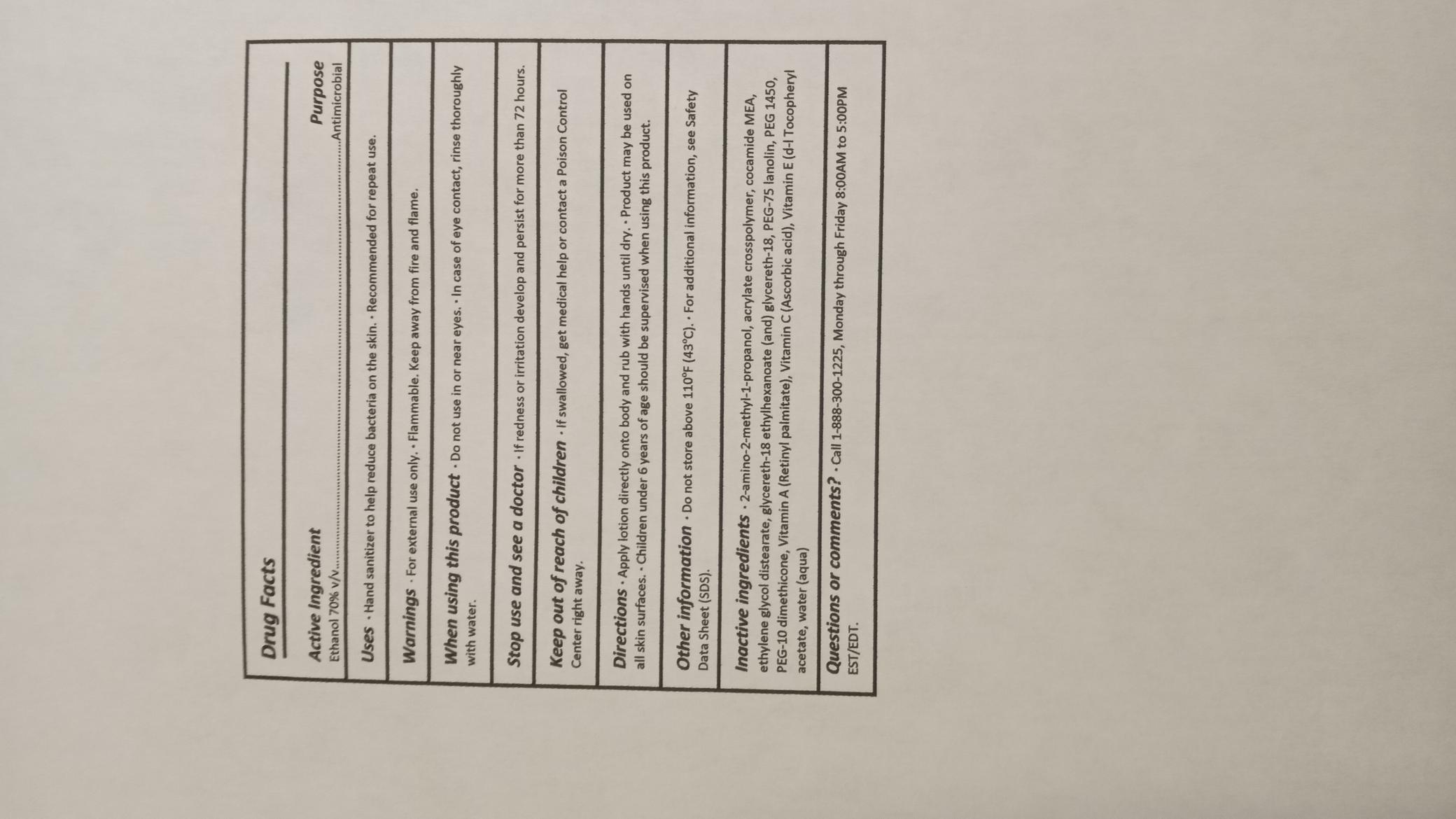 DRUG LABEL: Hand Recovery
NDC: 70741-007 | Form: Lotion
Manufacturer: Derma Glove
Category: otc | Type: HUMAN OTC DRUG LABEL
Date: 20251114

ACTIVE INGREDIENTS: ALCOHOL 70 mL/100 mL
INACTIVE INGREDIENTS: Water 20 mL/100 mL

ACTIVE INGREDIENT

Ethanol 70% v/v

PURPOSE

Antimicrobial

WARNINGS

For external use only. Flammable. Keep away from children.

Do not use in or near eyes. In case of eye contact, rinse thoroughly with water.

STOP USE

If redness or irritation develop and persist for more than 72 hours.

KEEP OUT OF REACH OF CHILDREN

If swallowed, get medical help or contact a Poison Control Center right away.

DOSAGE AND ADMINISTRATION

Apply lotion directly onto body and rub with hands until dry. Product may be used on all skin surfaces. Children under 6 years of age should be supervised when using this product.

INDICATIONS AND USAGE

Apply lotion directly onto body and rub with hands until dry. Product may be used on all skin surfaces. Children under 6 years of age should be supervised when using this product.

OTHER SAFETY INFORMATION

Do not store above 110oF (43oC). For additional information, see Safety Data Sheet (SDS).

INACTIVE INGREDIENT

Glycereth-18 (and) glycereth-18 ethylhexanoate, PEG-10 dimethicone, PEG-75 lanolin, ethylene glycol distearate, acrylate crosspolymer, 2-amino-2-methyl-1-propanol, water (aqua), PEG 1450, cocamide MEA

QUESTIONS

Call 1-888-300-1225, Monday through Friday 8:00AM to 5:00PM EST/EDT.